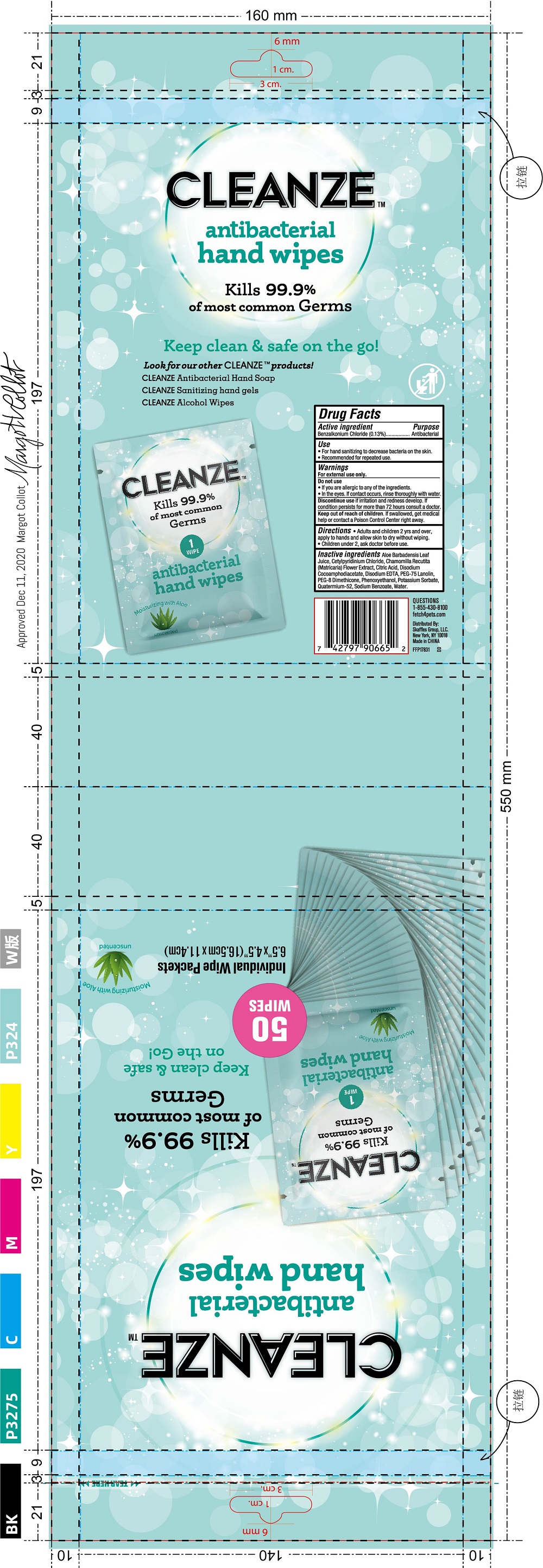 DRUG LABEL: Antibacterial Hand Wipes
NDC: 77720-019 | Form: CLOTH
Manufacturer: Skaffles Group Limited Liability Company
Category: otc | Type: HUMAN OTC DRUG LABEL
Date: 20210115

ACTIVE INGREDIENTS: BENZALKONIUM CHLORIDE 0.13 g/100 g
INACTIVE INGREDIENTS: WATER; QUATERNIUM-52; PEG-75 LANOLIN; ALOE VERA LEAF; CITRIC ACID MONOHYDRATE; POTASSIUM SORBATE; CETYLPYRIDINIUM CHLORIDE; PEG-8 DIMETHICONE; DISODIUM COCOAMPHODIACETATE; DISODIUM EDTA-COPPER; CHAMOMILE; PHENOXYETHANOL; SODIUM BENZOATE

77720-019 CLEANZE Antibacterial Hand Wipes 0.13% BENZALKONIUM CHLORIDE

Active Ingredient

Benzalkonium Chloride 0.13%

Purpose

Antibacterial

USE

For external use only .

For hand washing to decrease bacteria on the skin.
Recommended for repeated use.

Warning

For external use only.

Do not use
If you are allergic to any of the ingredients. In the eyes; if contact occurs, rinse thoroughly with water.
Discontinue use if irritation and redness develop. If condition persists for more than 72 hours consult a doctor.

Keep out of reach of children. lf swallowed, get medical help or contact a Poison Control Center right away.

Directions

Directions● Adults and children 2 yrs and over,
apply to hands and allow skin to dry without wiping.
●Children under 2, ask doctor before use.

Inactive ingredients

Aloe Barbadensis Leaf Juice, Cetylpyridinium Chloride, Chamomilla Recutita(Matricaria)Flower Extract, Citric Acid, Disodium Cocoamphodiacetate, Disodium EDTA, PEG-75 Lanolin,PEG-8Dimethicone,Phenoxyethanol,Potassium Sorbate, Quatermium-52, Sodium Benzoate, Water.